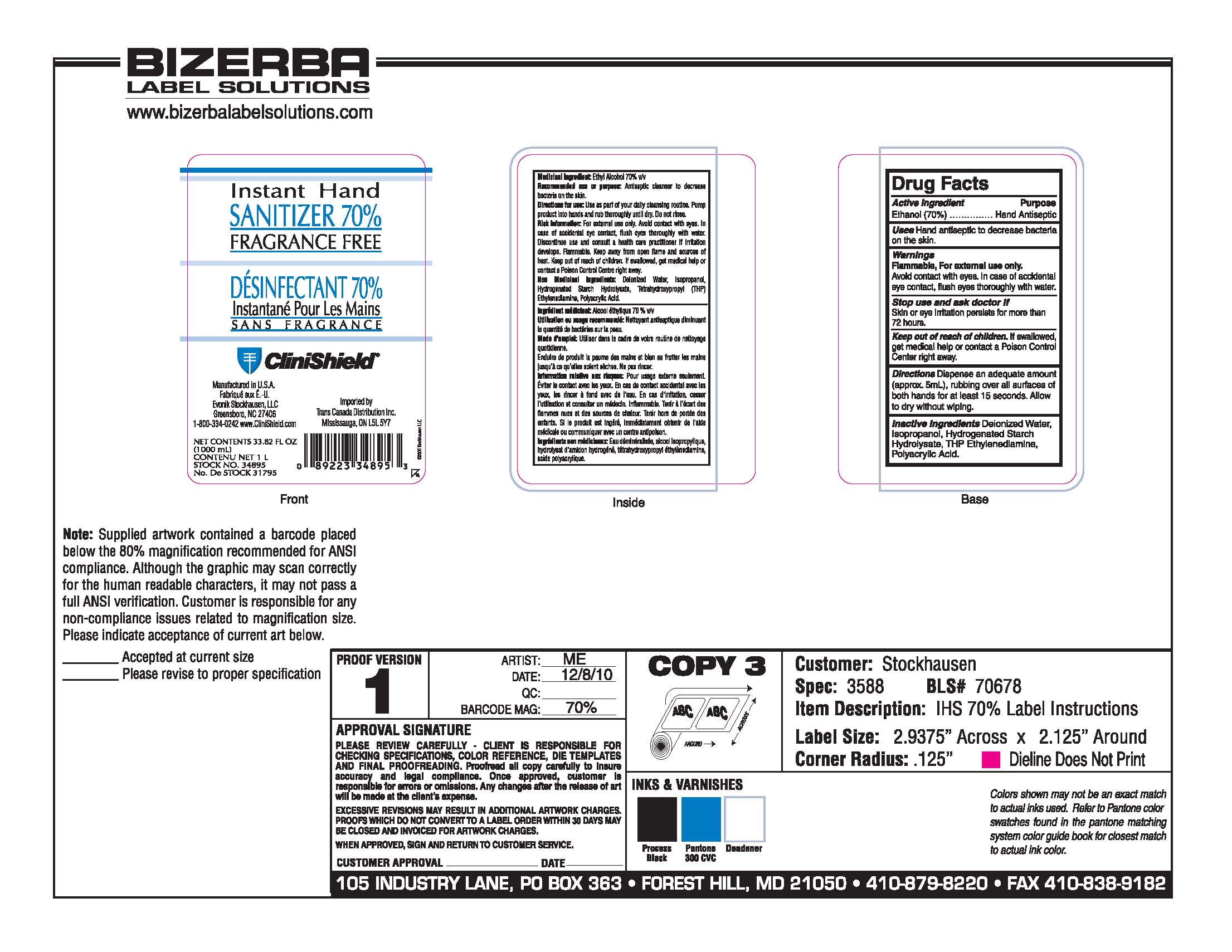 DRUG LABEL: CliniShield Instant Hand Sanitizer Fragrance Free
NDC: 64064-0002 | Form: GEL
Manufacturer: Evonik Stockhausen, LLC
Category: otc | Type: HUMAN OTC DRUG LABEL
Date: 20110120

ACTIVE INGREDIENTS: Alcohol 70 mL/100 mL
INACTIVE INGREDIENTS: Water; Isopropyl Alcohol; Edetol

Drug Facts

Active Ingredient

Ethanol (70%)

Purpose

Hand Antiseptic

Uses

Hand antiseptic to decrease bacteria on the skin.

Warnings

Flammable, For external use only.

Avoid contact with eyes. In case of accidental eye contact, flush eyes thorough with water.

Stop use and ask doctor if

Skin or eye irritation persists for more than 72 hours.

Keep out of reach of children. If swallowed, get medical help or contact a Poison Control Center right away.

Directions

Dispense an adequate amount (approx 5 mL), rubbing over all surfaces of both hands for at least 15 seconds. Allow to dry without wiping.

Inactive Ingredients

Deionized Water, Isopropanol, Hydrogenated Starch Hydrolysate, THP Ethylenediamine, Polyacrylic Acid

Principal Display Panel

Instant Hand

Sanitizer 70%

Fragrance Free

Desinfectant 80%

Instantane Pour Les Mains

Sans Fragrance

CliniShield

Manufactured in U.S.A.

Fabrique Aux E.-U.

Evonik Stockhausen, LLC

Greensboro, NC 27406

1-800-334-0242 www.CliniShield.com

Imported by Trans Canada Distribution Inc.

Mississauga, ON L5L 5Y7

Net Contents 33.82 Fl Oz

(1000 mL)

Contenu Net 1 L

Stock No. 34895

No. De Stock 31795